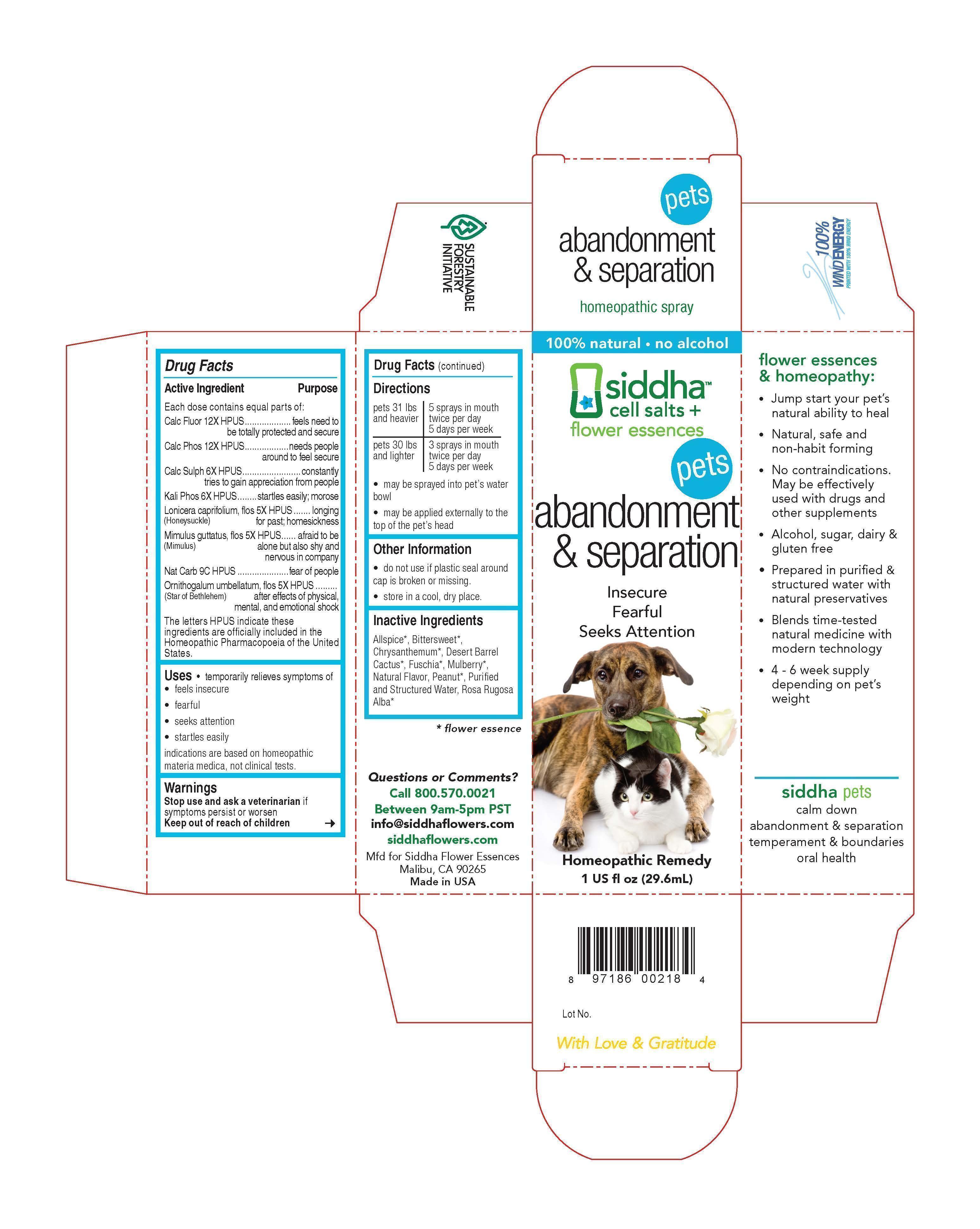 DRUG LABEL: abandonment and separation
NDC: 69779-021 | Form: SPRAY
Manufacturer: Siddha Flower Essences LLC
Category: homeopathic | Type: OTC ANIMAL DRUG LABEL
Date: 20150409

ACTIVE INGREDIENTS: CALCIUM FLUORIDE  12 [hp_X]/29.6 mL; TRIBASIC CALCIUM PHOSPHATE 12 [hp_X]/29.6 mL; CALCIUM SULFATE ANHYDROUS  6 [hp_X]/29.6 mL; POTASSIUM PHOSPHATE, DIBASIC  6 [hp_X]/29.6 mL; LONICERA CAPRIFOLIUM FLOWERING TOP  5 [hp_X]/29.6 mL; MIMULUS GUTTATUS FLOWERING TOP  5 [hp_X]/29.6 mL; SODIUM CARBONATE 9 [hp_C]/29.6 mL; ORNITHOGALUM UMBELLATUM FLOWERING TOP 5 [hp_X]/29.6 mL
INACTIVE INGREDIENTS: ALLSPICE    ; SOLANUM DULCAMARA FLOWER; CHRYSANTHEMUM X MORIFOLIUM FLOWER; PEANUT; WATER; ROSA RUGOSA FLOWER

Drug Facts

Active Ingredient

Each dose contains equal parts of:

Calc Fluor 12X HPUS
Calc Phos 12X HPUS
Calc Sulph 6X HPUS
Kali Phos 6X HPUS
Lonicera caprifolium, flos (Honeysuckle) 5X HPUS
Mimulus guttatus, flos (Mimulus) 5X HPUS
Nat Carb 9C HPUS
Ornithogalum umbellatum, flos (Star of Bethlehem) 5X HPUS

Purpose

Each dose contains equal parts of:
Calc Fluor 12X HPUS.....................................................................feels need to be totally protected and secure
Calc Phos 12X HPUS....................................................................needs people around to feel secure
Calc Sulph 6X HPUS......................................................................constantly tries to gain appreciation from people
Kali Phos 6X HPUS.......................................................................startles easily; morose
Lonicera caprifolium, flos (Honeysuckle) 5X HPUS...........................longing for past; homesickness
Mimulus guttatus, flos (Mimulus) 5X HPUS......................................afraid to be alone but also shy and nervous in company
Nat Carb 9C HPUS........................................................................fear of people
Ornithogalum umbellatum, flos (Star of Bethlehem) 5X HPUS...........after effects of physical, mental, and emotional shock
The letters HPUS indicate these ingredients are officially included in the Homeopathic Pharmacopoeia of the United States.

Uses

- temporarily relieves symptoms of
- feels insecure
- fearful
- seeks attention
- startles easily

indications are based on homeopathic materia medica, not clinical tests.

Warnings

Stop use and ask a veterinarian if symptoms persist or worsen

Keep out of reach of children

Directions

pets 31 lbs and heavier | 5 sprays in mouth twice per day 5 days per week
pets 30 lbs and lighter | 3 sprays in mouth twice per day 5 days per week

- may be sprayed into pet's water bowl
- may be applied externally to the top of pet's head

Other Information

- do not use if plastic seal around cap is broken or missing.
- store in a cool, dry place.

Inactive Ingredients

Allspice*, Bittersweet*, Chrysanthemum*, Desert Barrel Cactus*, Fuschia*, Mulberry*, Natural Flavor, Peanut*, Purified and Structured Water, Rosa Rugosa Alba*

*flower essence

Questions or Comments?
Call 800.570.0021
Between 9am-5pm PST
info@siddhaflowers.com
siddhaflowers.com
Mfd for Siddha Flower Essences
Malibu, CA 90265
Made in USA

Side Panel

flower essences and homeopathy:

- Jump start your pet's natural ability to heal
- Natural, safe and non-habit forming
- No contraindications. May be effectively used with drugs and other supplements
- Alcohol, sugar, dairy and gluten free
- Prepared in purified and structured water with natural preservatives
- Blends time-tested natural medicine with modern technology
- 4 - 6 week supply depending on pet's weight

siddha pets
calm down
abandonment and separation
temperament and boundaries
oral health

Principal Display Panel

100% natural - no alcohol
siddha cell salts + flower essences
pets
abandonment and separation
Insecure
Fearful
Seeks Attention
Homeopathic Remedy
1 US fl oz (29.6mL)